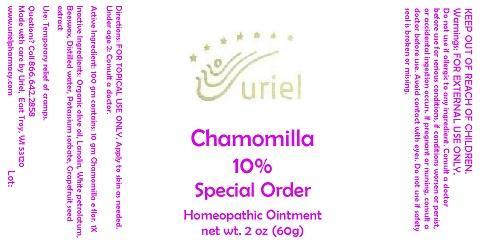 DRUG LABEL: Chamomilla 10 Special order
NDC: 48951-3188 | Form: OINTMENT
Manufacturer: Uriel Pharmacy Inc.
Category: homeopathic | Type: HUMAN OTC DRUG LABEL
Date: 20141125

ACTIVE INGREDIENTS: CHAMOMILE 1 [hp_X]/1 g
INACTIVE INGREDIENTS: OLIVE OIL; LANOLIN; PETROLATUM; YELLOW WAX; WATER; POTASSIUM SORBATE; CITRUS PARADISI SEED

Chamomilla 10 Special order

INDICATIONS AND USAGE

Directions: FOR TOPICAL USE ONLY.

DOSAGE AND ADMINISTRATION

Apply to skin as needed. Under age 2: Consult a doctor.

Active Ingredient: 100 gm contains: 10 gm Chamomilla e flor. 1X

INACTIVE INGREDIENT

Inactive Ingredients: Organic olive oil, Lanolin, White petrolatum, Beeswax, Distilled water, Potassium sorbate, Grapefruit seed extract

PURPOSE

Use: Temporary relief of cramps.

KEEP OUT OF REACH OF CHILDREN.

WARNINGS

Warnings: FOR EXTERNAL USE ONLY. Do not use if allergic to any ingredient. Consult a doctor before use for serious conditions, if conditions worsen or persist, or accidental ingestion occurs. If pregnant or nursing, consult a doctor before use. Avoid contact with eyes. Do not use if safety seal is broken or missing.

QUESTIONS

Questions? Call 866.642.2858 Made with care by Uriel, East Troy, WI 53120 www.urielpharmacy.com